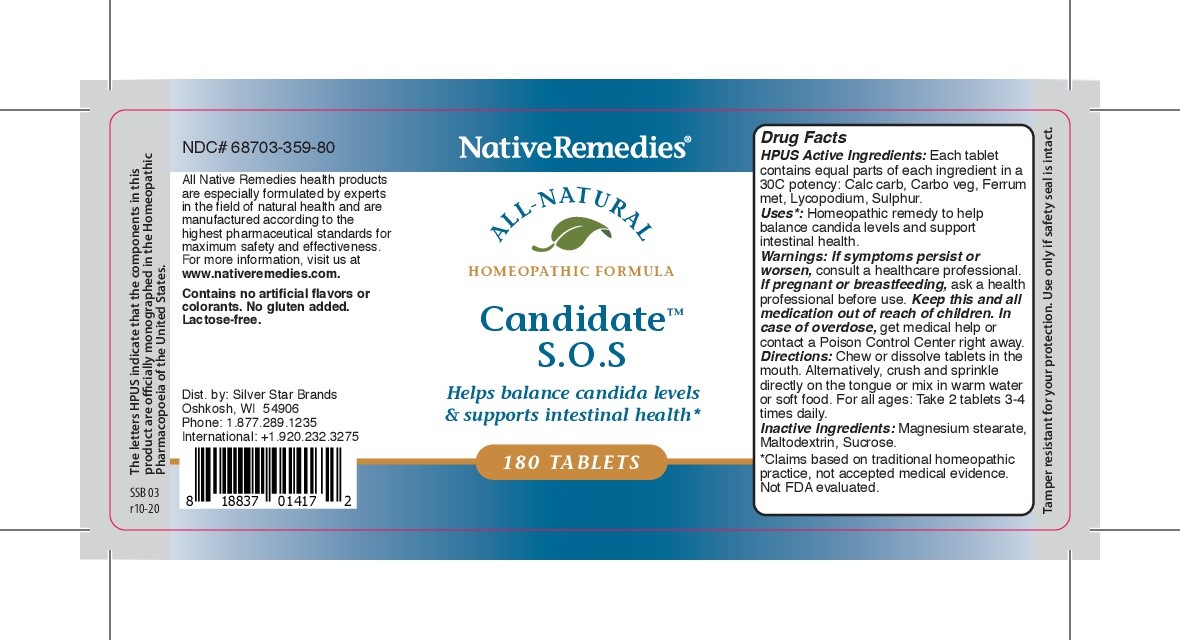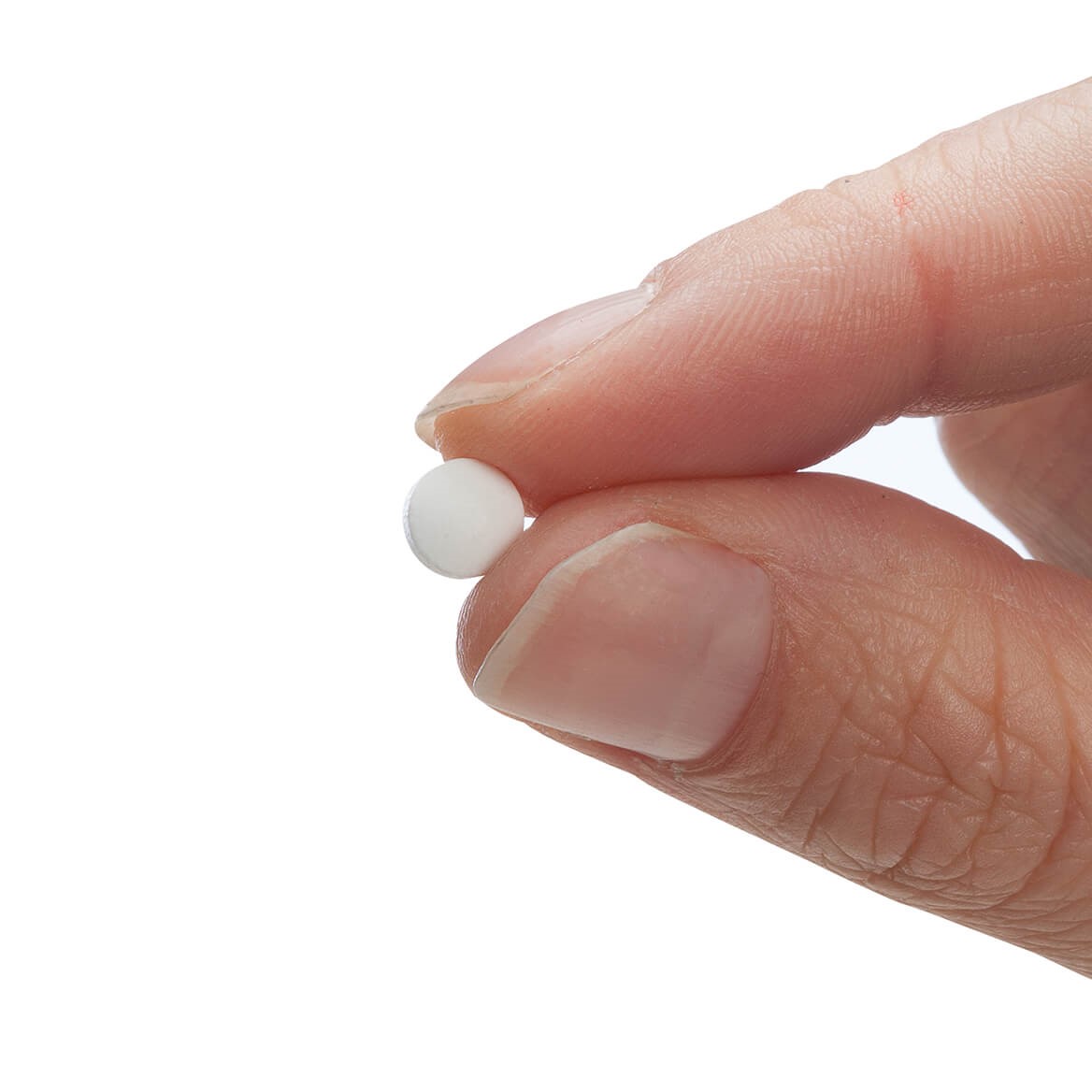 DRUG LABEL: Candidate S.O.S
NDC: 68703-359 | Form: TABLET
Manufacturer: Silver Star Brands
Category: homeopathic | Type: HUMAN OTC DRUG LABEL
Date: 20250101

ACTIVE INGREDIENTS: OYSTER SHELL CALCIUM CARBONATE, CRUDE 30 [hp_C]/180 1; ACTIVATED CHARCOAL 30 [hp_C]/180 1; LYCOPODIUM CLAVATUM SPORE 30 [hp_C]/180 1; SULFUR 30 [hp_C]/180 1; IRON 30 [hp_C]/180 1
INACTIVE INGREDIENTS: MALTODEXTRIN; MAGNESIUM STEARATE; SUCROSE

NativeRemedies® Candidate™ S.O.S.

HPUS Active Ingredients: Each tablet contains equal parts of each ingredient in a 30C potency: Calc carb, Carbo veg, Gerru met, Lycopodium, Sulphur.

Uses*:

Uses*: Homeopathic remedy to help balance candida levels and support intestinal health.

*Claims based on traditional homeopathic practice, not accepted medical evidence. Not FDA evaluated.

Warnings

Warnings: If symptoms persist or worsen, consult a healthcare professional. If pregnant or breastfeeding, ask a health professional before use. Keep this and all medication out of reach of children. In case of overdose, get medical help or contact a Poison Control Center right away.

Directions

Directions: Chew or dissolve tablets in the moth. Alternatively, crush and sprinkle directly on the tongue or mix in warm water or soft food. For all ages: Take 2 tablets 3-4 times daily.

OTHER SAFETY INFORMATION

Tamper resistant for your safety. Use only if safetey seal is intact.

Contains no artificial flavors or colorants. No gluten added. Lactose-free.

Inactive Ingredients

Inactive ingredients: Magnesium stearate, Maltodextrin, Sucrose.

KEEP OUT OF REACH OF CHILDREN

Keep this and all medication out of reach of children.

PREGNANCY OR BREAST FEEDING

If pregnant or breastfeeding, ask a health professional before use.

PURPOSE

Helps balance candida levels & supports intestinal health*

*Claims based on traditional homeopathic practice, not accepted medical evidence. Not FDA evaluated.